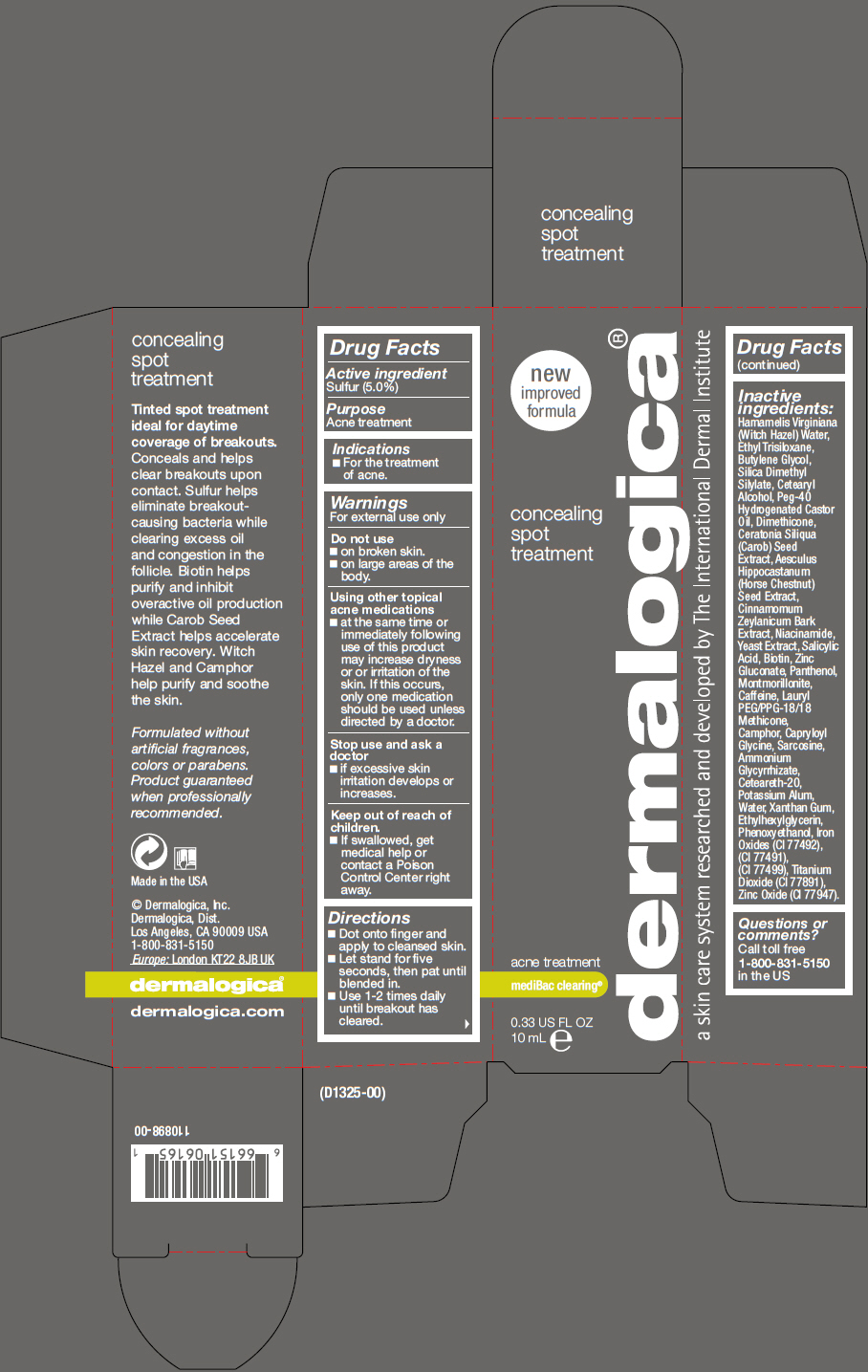 DRUG LABEL: Concealing Spot Treatment
NDC: 68479-005 | Form: LOTION
Manufacturer: Dermalogica, Inc.
Category: otc | Type: HUMAN OTC DRUG LABEL
Date: 20151119

ACTIVE INGREDIENTS: SULFUR 50 mg/1 mL
INACTIVE INGREDIENTS: HAMAMELIS VIRGINIANA TOP WATER; ETHYL TRISILOXANE; BUTYLENE GLYCOL; SILICA DIMETHYL SILYLATE; CETOSTEARYL ALCOHOL; POLYOXYL 40 HYDROGENATED CASTOR OIL; DIMETHICONE; HORSE CHESTNUT; CINNAMON BARK OIL; NIACINAMIDE; YEAST, UNSPECIFIED; SALICYLIC ACID; BIOTIN; ZINC GLUCONATE; PANTHENOL; MONTMORILLONITE; CAFFEINE; LAURYL PEG/PPG-18/18 METHICONE; CAMPHOR (SYNTHETIC); CAPRYLOYL GLYCINE; SARCOSINE; AMMONIUM GLYCYRRHIZATE; POLYOXYL 20 CETOSTEARYL ETHER; POTASSIUM ALUM; WATER; XANTHAN GUM; ETHYLHEXYLGLYCERIN; PHENOXYETHANOL; FERRIC OXIDE YELLOW; FERRIC OXIDE RED; FERROSOFERRIC OXIDE; TITANIUM DIOXIDE; ZINC OXIDE

Concealing Spot Treatment

Drug Facts

Active ingredient

Sulfur (5.0%)

Purpose

Acne treatment

Indications

- For the treatment of acne.

Warnings

For external use only

Do not use

- on broken skin.
- on large areas of the body.

Using other topical acne medications

- at the same time or immediately following use of this product may increase dryness or or irritation of the skin. If this occurs, only one medication should be used unless directed by a doctor.

Stop use and ask a doctor

- if excessive skin irritation develops or increases.

Keep out of reach of children

- If swallowed, get medical help or contact a Poison Control Center right away.

Directions

- Dot onto finger and apply to cleansed skin.
- Let stand for five seconds, then pat until blended in.
- Use 1-2 times daily until breakout has cleared.

Inactive ingredients

Hamamelis Virginiana (Witch Hazel) Water, Ethyl Trisiloxane, Butylene Glycol, Silica Dimethyl Silylate, Cetearyl Alcohol, Peg-40 Hydrogenated Castor Oil, Dimethicone, Ceratonia Siliqua (Carob) Seed Extract, Aesculus Hippocastanum (Horse Chestnut) Seed Extract, Cinnamomum Zeylanicum Bark Extract, Niacinamide, Yeast Extract, Salicylic Acid, Biotin, Zinc Gluconate, Panthenol, Montmorillonite, Caffeine, Lauryl PEG/PPG-18/18 Methicone, Camphor, Capryloyl Glycine, Sarcosine, Ammonium Glycyrrhizate, Ceteareth-20, Potassium Alum, Water, Xanthan Gum, Ethylhexylglycerin, Phenoxyethanol, Iron Oxides (CI 77492), (CI 77491), (CI 77499), Titanium Dioxide (CI 77891), Zinc Oxide (CI 77947).

Questions or comments?

Call toll free 1-800-831-5150 in the US

PRINCIPAL DISPLAY PANEL - 10 mL Tube Carton

new
improved
formula

concealing
spot
treatment

acne treatment

mediBac clearing®

0.33 US FL OZ
10 mL e

dermalogica®